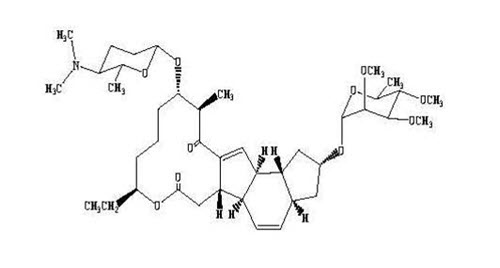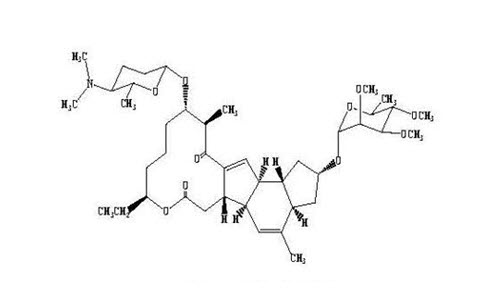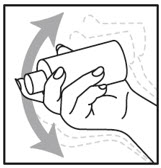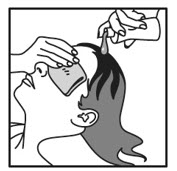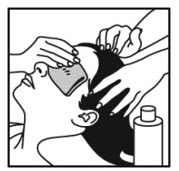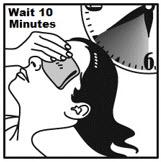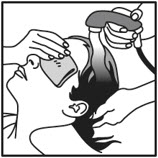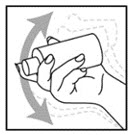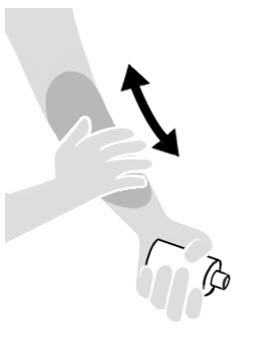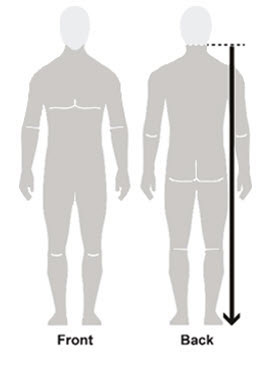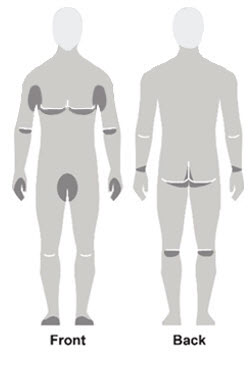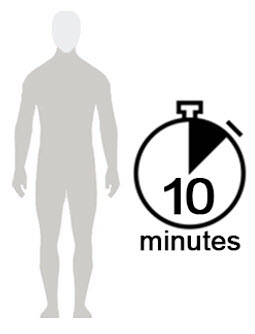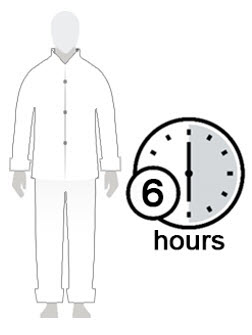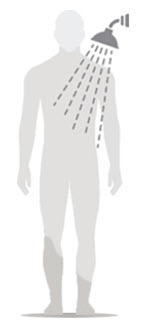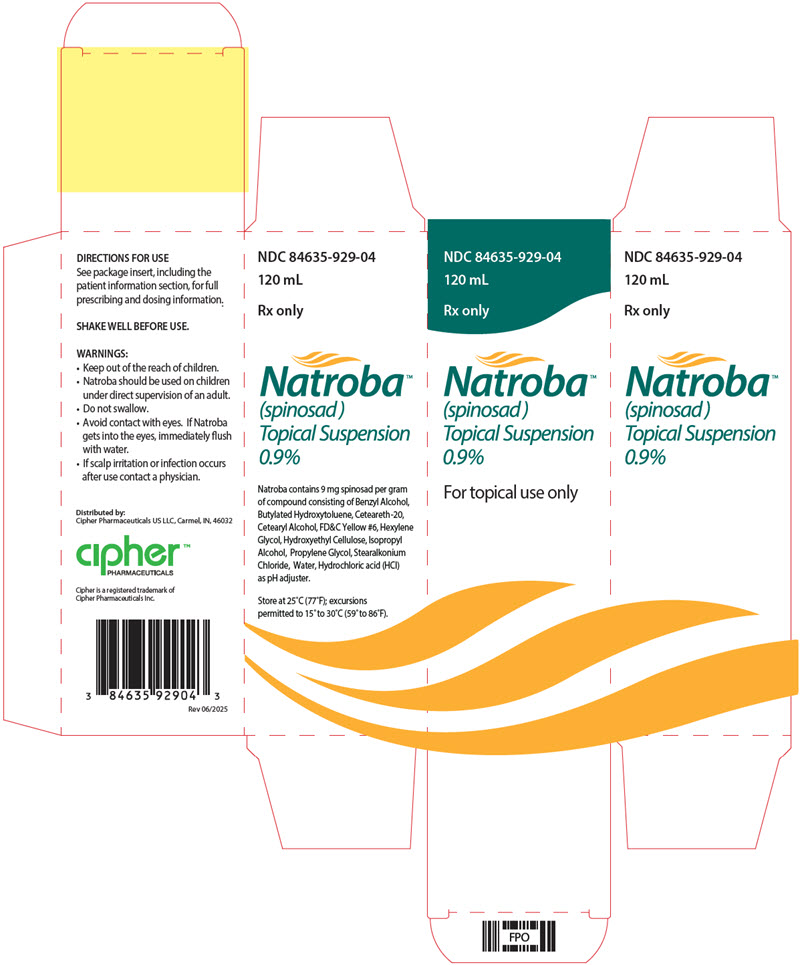 DRUG LABEL: Natroba
NDC: 84635-929 | Form: SUSPENSION
Manufacturer: Cipher Pharmaceuticals Inc.
Category: prescription | Type: HUMAN PRESCRIPTION DRUG LABEL
Date: 20251119

ACTIVE INGREDIENTS: SPINOSAD 9 mg/1 mL
INACTIVE INGREDIENTS: BENZYL ALCOHOL; BUTYLATED HYDROXYTOLUENE; POLYOXYL 20 CETOSTEARYL ETHER; CETOSTEARYL ALCOHOL; FD&C YELLOW NO. 6; HEXYLENE GLYCOL; HYDROXYETHYL CELLULOSE (2000 MPA.S AT 1%); ISOPROPYL ALCOHOL; PROPYLENE GLYCOL; STEARALKONIUM CHLORIDE; WATER; HYDROCHLORIC ACID

HIGHLIGHTS OF PRESCRIBING INFORMATION

These highlights do not include all the information needed to use NATROBA Topical Suspension safely and effectively. See full prescribing information for NATROBA Topical Suspension.
NATROBA (spinosad) topical suspension
Initial U.S. Approval: 2011

1 INDICATIONS AND USAGE

NATROBA is a pediculicide indicated for the topical treatment of head lice infestations in adult and pediatric patients 6 months of age and older. (1.1)

NATROBA is a scabicide indicated for the topical treatment of scabies infestations in adult and pediatric patients 4 years of age and older. (1.2)

2 DOSAGE AND ADMINISTRATION

- For topical use only. Not for oral, ophthalmic, or intravaginal use. (2)
- Treatment of head lice infestations (2.2):
  - Shake bottle well
  - Apply a sufficient amount to cover dry scalp, then apply to dry hair
  - Rinse off with warm water after 10 minutes
  - Repeat treatment only if live lice are seen 7 days after first treatment
- Treatment of scabies infestations (2.3):
  - Shake bottle well
  - Apply product to skin by rubbing it in to completely cover the body from the neck down to the soles of the feet
  - Patients with balding scalp should also apply product to the scalp, hairline, temples, and forehead
  - Allow to absorb in the skin and dry for 10 minutes before getting dressed
  - Leave on the skin for at least 6 hours before showering or bathing

3 DOSAGE FORMS AND STRENGTHS

Topical suspension: 0.9% w/w (3)

4 CONTRAINDICATIONS

None. (4)

5 WARNINGS AND PRECAUTIONS

Benzyl Alcohol Toxicity: Not recommended in infants below the age of 6 months; potential for increased systemic absorption. (5.1)

6 ADVERSE REACTIONS

Most common adverse events for lice treatment (>1%) were application site erythema and ocular erythema. (6.1)

Most common adverse reactions for scabies treatment (>1%) were application site irritation (pain and burning) and dry skin. (6.1)

To report SUSPECTED ADVERSE REACTIONS, contact Cipher Pharmaceuticals US LLC at 1-855-628-7622 or FDA at 1-800-FDA-1088 or www.fda.gov/medwatch.

FULL PRESCRIBING INFORMATION

1 INDICATIONS AND USAGE

1.1 Head Lice Infestations

NATROBA is indicated for the topical treatment of head lice infestations in adult and pediatric patients 6 months of age and older.

Adjunctive Measures for Head Lice Infestations

NATROBA should be used in the context of an overall lice management program:

- Wash in hot water or dry-clean all recently worn clothing, hats, used bedding and towels.
- Wash personal care items such as combs, brushes and hair clips in hot water.
- A fine-tooth comb or special nit comb may be used to remove dead lice and nits.

1.2 Scabies Infestations

NATROBA is indicated for the topical treatment of scabies infestations in adult and pediatric patients 4 years of age and older.

Adjunctive Measures for Scabies Infestations

- Wash in hot water or dry-clean any bedding, clothing and towels used by anyone having scabies.

2 DOSAGE AND ADMINISTRATION

2.1 Important Administration Instructions

- For topical use only. NATROBA is not for oral, ophthalmic, or intravaginal use.
- Avoid contact with eyes. If NATROBA gets in or near the eyes, rinse thoroughly with water.

2.2 Treatment of Head Lice Infestations

- Shake bottle well.
- Apply a sufficient amount of NATROBA to cover dry scalp, then apply to dry hair. Depending on hair length, apply up to 120 mL (one bottle) to adequately cover scalp and hair.
- Leave on for 10 minutes, then thoroughly rinse off with warm water.
- Wash hands after use.
- If live lice are seen 7 days after the first treatment, a second treatment should be applied.
- Apply NATROBA on pediatric patient only under direct supervision of an adult [see Warnings and Precautions (5.1)].

2.3 Treatment of Scabies Infestations

- Shake bottle well.
- Apply a sufficient amount of NATROBA to skin to completely cover the body from the neck to the toes (including the soles of the feet).
- For patients with balding scalp, also apply product to the scalp, hairline, temples, and forehead.
- Allow to absorb into the skin and dry for 10 minutes before getting dressed.
- Leave on the skin for at least 6 hours before showering or bathing.
- Apply NATROBA on pediatric patient only under direct supervision of an adult.

3 DOSAGE FORMS AND STRENGTHS

Topical suspension: 0.9% w/w; each gram contains 9 mg of spinosad in a viscous, slightly opaque (white soft particles may be visible), light orange-colored suspension in 120 mL bottles.

4 CONTRAINDICATIONS

None.

5 WARNINGS AND PRECAUTIONS

5.1 Benzyl Alcohol Toxicity

NATROBA contains benzyl alcohol and is not approved for use in neonates and infants below the age of 6 months. Systemic exposure to benzyl alcohol has been associated with serious adverse reactions and death in neonates and low birth-weight infants when administered intravenously [See Use in Specific Populations (8.4)].

6 ADVERSE REACTIONS

6.1 Clinical Studies Experience

Because clinical studies are conducted under widely varying conditions, adverse reaction rates observed in the clinical studies of a drug cannot be directly compared to rates in the clinical studies of another drug and may not reflect the rates observed in clinical practice.

Head Lice Infestations

NATROBA was studied in two randomized, active-controlled trials (N=552) in subjects with head lice; Table 1 presents selected adverse events, regardless of relationship to NATROBA, that occurred in at least 1% of subjects.

Table 1: Selected Adverse Events Occurring in at least 1% of Subjects with Head Lice Infestation
Signs | Natroba (N=552) | Permethrin 1% (N=457)
Application site erythema | 17 (3%) | 31(7%)
Ocular erythema | 12 (2%) | 15 (3%)
Application site irritation | 5 (1%) | 7 (2%)

Other less common reactions (less than 1% but more than 0.1%) were application site dryness, application site exfoliation, alopecia, and dry skin.

Scabies Infestations

NATROBA was studied in three randomized, double-blind, vehicle-controlled trials (Trial 1, Trial 2, and Trial 3) in 592 subjects with scabies infestation, of which 165 were ages 4-17 and 427 were adults. Subjects received a single application of NATROBA to the skin from the neck to the soles of the feet, which was washed off after a minimum of 6 hours. Table 2 presents adverse reactions related to NATROBA treatment that occurred in at least 1% of subjects.

Table 2: Adverse Reactions Occurring in at least 1% of Subjects with Scabies Infestation (Trials 1, 2 and 3)
Signs | Natroba (N=322) | Vehicle (N=270)
Application site irritation [Application site irritation also includes application site pain and burning sensation.] | 8 (3%) | 0 (0%)
Dry skin | 6 (2%) | 0 (0%)

8 USE IN SPECIFIC POPULATIONS

8.1 Pregnancy

Risk Summary

Spinosad, the active ingredient in NATROBA, is not absorbed systemically following topical application, and maternal use is not expected to result in fetal exposure to the drug. NATROBA contains benzyl alcohol. Topical benzyl alcohol is unlikely to be absorbed through the skin in clinically relevant amounts; therefore, maternal use is not expected to result in fetal exposure to the drug [see Clinical Pharmacology (12.3)].

In animal reproduction studies, no adverse embryofetal effects were seen at oral doses of spinosad up to 200 mg/kg/day in pregnant rats or 50 mg/kg/day in pregnant rabbits administered during the period of organogenesis (see Data). The available data do not allow the calculation of relevant comparisons between the systemic exposure of spinosad in animal studies to the systemic exposure that would be expected in humans after topical use of NATROBA.

The background risk of major birth defects and miscarriage for the indicated population is unknown. All pregnancies have a background risk for birth defect, loss, or other adverse outcomes. In the U.S. general population, the estimated background risk of major birth defects and miscarriage in clinically recognized pregnancies is 2 to 4% and 15 to 20%, respectively.

Data

Animal Data

Systemic embryofetal development studies were conducted in rats and rabbits. Oral doses of 10, 50 and 200 mg/kg/day spinosad were administered during the period of organogenesis (gestational days 6 – 15) to pregnant female rats. No adverse embryofetal effects were noted at any dose. Maternal toxicity occurred at 200 mg/kg/day. Oral doses of 2.5, 10, and 50 mg/kg/day spinosad were administered during the period of organogenesis (gestational days 7 – 19) to pregnant female rabbits. No adverse embryofetal effects were noted at any dose. Maternal toxicity occurred at 50 mg/kg/day.

A two-generation dietary reproduction study was conducted in rats. Oral doses of 3, 10, and 100 mg/kg/day spinosad were administered to male and female rats from 10-12 weeks prior to mating and throughout mating, parturition, and lactation. No reproductive/developmental toxicity was noted at doses up to 10 mg/kg/day. In the presence of maternal toxicity, increased dystocia in parturition, decreased gestation survival, decreased litter size, decreased pup body weight, and decreased neonatal survival occurred at a dose of 100 mg/kg/day.

8.2 Lactation

Risk Summary

Spinosad, the active ingredient in NATROBA, is not systemically absorbed by the mother following topical application. Therefore, breastfeeding is not expected to result in the exposure of the child to spinosad [see Clinical Pharmacology (12.3)]. Advise breastfeeding women to remove NATROBA from the breast with soap and water before breastfeeding to avoid direct infant exposure to NATROBA.

NATROBA contains benzyl alcohol. Topical benzyl alcohol is unlikely to be absorbed through the skin of breastfeeding women in clinically relevant amounts; therefore, breastfeeding is not expected to result in exposure of the infant to NATROBA [see Clinical Pharmacology (12.3)]. The developmental and health benefits of breastfeeding should be considered along with the mother's clinical need for NATROBA and any potential adverse effects on the breastfed child from NATROBA, or from the underlying maternal condition.

8.4 Pediatric Use

Head Lice Infestation

The safety and effectiveness of NATROBA for the topical treatment of head lice infestation have been established in pediatric patients 6 months of age and older [see Clinical Pharmacology (12.3) and Clinical Studies (14)].

NATROBA is not recommended in pediatric patients below the age of 6 months because of the potential for increased systemic absorption due to a high ratio of skin surface area to body mass and the potential for an immature skin barrier.

NATROBA contains benzyl alcohol. Intravenous administration of benzyl alcohol has been associated with serious adverse reactions and death in neonates and low birth-weight infants. The "gasping syndrome" (characterized by central nervous system depression, metabolic acidosis, gasping respirations, and high levels of benzyl alcohol and its metabolites found in the blood and urine) has been associated with benzyl alcohol dosages >99 mg/kg/day in neonates and low-birthweight infants when administered intravenously. Additional symptoms may include gradual neurological deterioration, seizures, intracranial hemorrhage, hematologic abnormalities, skin breakdown, hepatic and renal failure, hypotension, bradycardia, and cardiovascular collapse.

The minimum amount of benzyl alcohol at which toxicity may occur is not known. Premature and low-birthweight infants, as well as patients receiving high dosages of benzyl alcohol, may be more likely to develop toxicity [see Warning and Precautions (5.1)].

Scabies Infestation

The safety and effectiveness of NATROBA for the topical treatment of scabies infestation have been established in pediatric patients 4 years of age and older. Use of NATROBA in this age group is supported by Trial 1 and Trial 2 which included 165 pediatric subjects ages 4 to 17 years old with scabies infestation. The safety and efficacy were generally consistent between pediatric and adult patients. [see Clinical Pharmacology (12.3) and Clinical Studies (14)].

The safety and effectiveness of NATROBA have not been established in pediatric patients less than 4 years of age with scabies infestation.

8.5 Geriatric Use

Clinical studies of NATROBA did not include sufficient numbers of subjects aged 65 and over to determine whether they respond differently from younger subjects. Other reported clinical experience has not identified differences in responses between the elderly and younger patients.

10 OVERDOSAGE

No specific antidotes for spinosad overdosage are known. If oral ingestion occurs, contact Poison Control (1-800-222-1222) for latest recommendations and seek medical attention immediately.

11 DESCRIPTION

NATROBA (spinosad) is a slightly opaque, light orange-colored, viscous topical suspension.

NATROBA is a pediculicide and scabicide. Spinosad, the active ingredient, is derived from the fermentation of a soil actinomycete bacterium, Saccharopolyspora spinosa.

Spinosad is a mixture of spinosyn A and spinosyn D in a ratio of approximately 5 to 1 (spinosyn A to spinosyn D).

Spinosyn A: The chemical name is: 1H-as-Indaceno[3,2-d]oxacyclododecin-7,a5-dione, 2-[(6-deoxy-2,3,4-tri-O-methyl-alpha-L-mannopyranosyl)oxy]-13-[[2R,5S,6R)-5-(dimethylamino) tetrahydro-6-methyl-2H-pyran-2-yl]oxy]-9-ethyl-2,3,3a,5a,5b,6,9,10,11,12,13,14,16a,16b-tetradecahydro-14-methyl-, (2R,3aS,5aR,5bS,9S,13S,14R,16aS,16bR)-

Spinosyn D: The chemical name is: 1H-as-Indaceno[3,2-d]oxacyclododecin-7,15-dione, 2-[(6-deoxy-2,3,4-tri-O-methyl-alpha-L-mannopyranosyl)oxy]-13-[[2R,5S,6R)-5-(dimethylamino) tetrahydro-6-methyl-2H-pyran-2-yl]oxy]-9-ethyl-2,3,3a,5a,5b,6,9,10,11,12,13,14,16a,16b-tetradecahydro-4,14-dimethyl-, (2S,3aSR,5aS,5bS,9S,13S,14R,16aS,16bS)-

Spinosyn A (C41H65NO10)
MW 731.461

Spinosyn D (C42H67NO10)
MW 745.477

NATROBA contains 9 mg spinosad per gram in a vehicle consisting of Benzyl Alcohol, Butylated Hydroxytoluene, Ceteareth-20, Cetearyl Alcohol, FD&C Yellow #6, Hexylene Glycol, Hydroxyethyl Cellulose, Isopropyl Alcohol, Propylene Glycol, Stearalkonium Chloride, Water, Hydrochloric acid (HCl) as pH adjuster.

12 CLINICAL PHARMACOLOGY

12.1 Mechanism of Action

Spinosad causes neuronal excitation in insects. After periods of hyperexcitation, lice and mites become paralyzed and die.

12.2 Pharmacodynamics

The pharmacodynamics of NATROBA has not been studied.

12.3 Pharmacokinetics

Head Lice Infestations

An open-label, single-center trial was conducted over a period of seven days to determine the pharmacokinetic profile of spinosad 1.8% in pediatric subjects with head lice infestation. Fourteen (14) subjects, 4 – 15 years of age, with head lice were enrolled into the trial. All subjects applied a single topical (scalp) treatment of spinosad 1.8% for 10 minutes, after which the test article was washed off, and subjects underwent plasma sampling. Results demonstrated that spinosad was below the limit of quantitation (3 ng/mL) in all samples. Plasma concentration of benzyl alcohol was not determined in these subjects.

An open-label, two-center trial was conducted over a period of 23 days to determine the pharmacokinetic profile of spinosad 0.9% and the ingredient benzyl alcohol in pediatric subjects with a head lice infestation. Twenty-six (26) subjects between 6 months to 4 years of age were enrolled into the study per protocol. All subjects applied a single topical (scalp) treatment of spinosad 0.9% for 10 minutes, after which the test article was washed off, and subjects underwent plasma sampling over a 12 hour period. Plasma spinosad concentrations were below the limit of quantitation (3 ng/mL) in all samples.

Benzyl alcohol was quantifiable (above 1 µg/mL) in a total of 8 plasma samples in 6 out of 26 subjects (25%): four out of 12 subjects in the 6 months to <2 years age group and two out of 14 subjects in the 2 to 4 years age group. The highest observed concentration was 2.37 µg/mL. Benzyl alcohol concentrations at 12 hours post-treatment were below limit of quantification (1 µg/mL) for all subjects.

Scabies Infestations

An open-label multi-center trial was conducted to determine the pharmacokinetic profile of spinosad 0.9% and the ingredient benzyl alcohol in pediatric subjects with scabies infestation. The PK bioavailability study was completed in 19 pediatrics subjects 5 to 16 years of age. All subjects applied a single topical body treatment of spinosad 0.9% from the neck down to the soles of the feet and allowed treatment to remain on the body for a minimum of 6 hours after which the test article was washed off. Subjects underwent plasma sampling over a 12-hour period after treatment. Plasma spinosad concentrations were below the limit of quantification (3 ng/mL) in all samples.

Benzyl alcohol was quantifiable (above 1 µg/mL) in a total of 9 plasma samples in 6 out of 19 subjects (32%): in 3 out of 10 subjects in the 5 to 9 year age group and in 3 out of 9 subjects in the 10 to 16 years age group. The highest observed concentration was 3.94 µg/mL at 0.5 hours post-treatment but was below limit of quantification at 1 hour post-treatment for one subject in the 10 to 16 years age group. There were two subjects with a benzyl alcohol concentration at 3 hours post-treatment with the highest value of 3.53 µg/mL for one subject in the 5 to 9 years age group. Plasma concentrations were below limit of quantification (1 µg/mL) at 3 hours for all other subjects; no subject had measurable concentrations at the 6 and12 hour time points. The mean (SD) Cmax, Tmax, and AUC0-12h values for benzyl alcohol were 2.737 (1.107) µg/mL, 1.42 (1.242) hours, and 19.240 µg∙h/mL, respectively.

13 NONCLINICAL TOXICOLOGY

13.1 Carcinogenesis, Mutagenesis, Impairment of Fertility

In an oral (diet) mouse carcinogenicity study, spinosad was administered to CD-1 mice at doses of 0.0025, 0.008, and 0.036% in the diet (approximately 3.4, 11.4, and 50.9 mg/kg/day for males and 4.2, 13.8, and 67.0 mg/kg/day for females) for 18 months. No treatment-related tumors were noted in the mouse carcinogenicity study up to the highest doses evaluated in this study of 50.9 mg/kg/day in male mice and 13.8 mg/kg/day in female mice. Female mice treated with a dose of 67.0 mg/kg/day were not evaluated in this study due to high mortality.

In an oral (diet) rat carcinogenicity study, spinosad was administered to Fischer 344 rats at doses of 0.005, 0.02, 0.05, and 0.1% in the diet (approximately 2.4, 9.5, 24.1 and 49.4 mg/kg/day for males and 3.0, 12.0, 30.1 and 62.8 mg/kg/day for females) for 24 months. No treatment-related tumors were noted in the rat carcinogenicity study in male or female rats up to the highest doses evaluated in this study of 24.1 mg/kg/day in male rats and 30.1 mg/kg/day in female rats. Rats in the highest dose group in this study were not evaluated due to high mortality.

Spinosad demonstrated no evidence of mutagenic or clastogenic potential based on the results of four in vitro genotoxicity tests (Ames assay, mouse lymphoma L5178Y assay, Chinese hamster ovary cell chromosome aberration assay, and rat hepatocyte unscheduled DNA synthesis assay) and one in vivo genotoxicity test (mouse bone marrow micronucleus assay).

Oral administration of spinosad (in diet) to rats, throughout mating, gestation, parturition and lactation, demonstrated no effects on growth, fertility or reproduction, at doses up to 10 mg/kg/day [see Use In Specific Populations (8.1)].

14 CLINICAL STUDIES

14.1 Head Lice Infestations

Two multicenter, randomized, investigator-blind, active-controlled trials were conducted in 1038 subjects 6 months of age and older with head lice infestation. A total of 552 subjects were treated with NATROBA. For the evaluation of efficacy, the youngest subject from each household was considered to be the primary subject of the household, and other members in the household were enrolled in the study as secondary subjects and evaluated for all safety parameters.

In Study 1, 91 primary subjects were randomized to NATROBA, and 89 primary subjects were randomized to permethrin 1%. In Study 2, 83 and 84 primary subjects were randomized to NATROBA and permethrin 1%, respectively.

In both trials, all subjects who were treated on Day 0 returned for efficacy evaluation at Day 7. Subjects with live lice present at Day 7 received a second treatment. Subjects who were lice free on Day 7 were to return on Day 14 for evaluation. Subjects with live lice and who received a second treatment were to return on Days 14 and 21.

Efficacy was assessed as the proportion of primary subjects who were free of live lice 14 days after the final treatment. Table 3 contains the proportion of primary subjects who were free of live lice in each of the two trials.

Table 3. Proportion of Subjects Free of Live Lice 14 days After Last Treatment
Study 1 |  | Study 2
Natroba (N=91) | Permethrin 1% (N=89) | Natroba (N=83) | Permethrin 1% (N=84)
77 (84.6%) | 40 (44.9%) | 72 (86.7%) | 36 (42.9%)

14.2 Scabies Infestations

Two multicenter, randomized, double-blind, vehicle-controlled trials (Trial 1 [NCT02485717] and Trial 2 [NCT02485704]) were conducted in subjects from 206 households in which at least one household member 4 years of age or older had an active scabies infestation. An active scabies infestation was defined as the presence of clinical signs and symptoms (evidence of burrows or presence of inflammatory/ noninflammatory lesions and pruritus) as well as microscopic evidence from a skin scraping or dermatoscopy to demonstrate the presence of mites, eggs, and/or scybala. All members of the household were treated with the same randomized treatment (NATROBA or vehicle), whether or not the household member had an active scabies infestation. Subjects applied a single application of NATROBA or vehicle on Day 1 and returned for evaluation on Day 28.

The two studies enrolled 533 adult and pediatric subjects 4 years of age and older. A total of 286 subjects (212 adults and 74 pediatrics) were treated with NATROBA and 247 subjects (176 adults and 71 pediatrics) were treated with vehicle. For the evaluation of efficacy, the youngest subject from each household with an active scabies infestation was considered to be the primary subject of the household, and other members in the household were enrolled in the trial as secondary subjects and evaluated for all safety parameters. In Trial 1, 43 primary subjects were randomized to NATROBA, and 43 primary subjects were randomized to vehicle. In Trial 2, 62 and 58 primary subjects were randomized to NATROBA and vehicle, respectively.

Efficacy was assessed as the proportion of primary subjects who achieved complete cure 28 days after treatment. Complete cure is defined as a demonstration of clinical cure (all signs and symptoms have completely resolved, including burrows, inflammatory/non-inflammatory lesions and pruritus) and microscopic or dermatoscopic cure demonstrating the absence of mites, eggs, and/or scybala, and negative dermatoscopy for burrows. Table 4 contains the proportion of primary subjects who achieved complete cure in each of the two trials.

Table 4. Proportion of Primary Subjects with Scabies Infestation who Achieved Complete Cure 28 Days After Treatment
Trial 1 |  |  | Trial 2
Natroba N=43 | Vehicle N=43 | Estimated Difference 95% CI | Natroba N=62 | Vehicle N=58 | Estimated Difference 95% CI
30 (69.8%) | 20 (46.5%) | 22.7% (1.8%, 43.5%) | 52 (83.9%) | 20 (34.5%) | 49.7% (36.0%, 63.5%)
CI= Confidence Interval

16 HOW SUPPLIED/STORAGE AND HANDLING

How Supplied

NATROBA (spinosad) topical suspension, 0.9% w/w; each gram contains 9 mg of spinosad in a slightly opaque (white soft particles may be visible), light orange-colored, viscous liquid, supplied in 4 oz (120 mL) high density polyethylene (HDPE) bottles. NDC 84635-929-04

Storage and Handling

Store at 25° C (77° F); excursions permitted to 15° to 30° C (59° to 86° F).

17 PATIENT COUNSELING INFORMATION

Advise patients to read the FDA-approved patient labeling (Patient Information)

Important Administration Instructions

Instruct the patient to:

- Shake bottle well immediately prior to application.
- Do not swallow.
- Avoid contact with eyes. If NATROBA gets in or near the eyes, rinse thoroughly with water.
- Apply NATROBA on pediatric patient only under direct supervision of an adult.
- If skin/scalp irritation occurs after use, contact your physician [see Adverse Reactions (6.1)].

Head Lice Infestation Treatment

- Apply NATROBA only on dry scalp and dry scalp hair.
- Repeat treatment only if live lice are seen seven (7) days after first treatment.
- Wash hands after applying NATROBA.

Scabies Infestation Treatment

- Apply NATROBA to completely cover the body from the neck to the toes (including the soles of the feet).
- For patients with balding scalp, also apply product to the scalp, hairline, temples, and forehead.
- Allow it to absorb in the skin and dry for 10 minutes before getting dressed.
- Leave on the skin for at least 6 hours before showering or bathing.
- Wash your hands after applying NATROBA to someone else.
- For breastfeeding women, remove NATROBA from the breast with soap and water before breastfeeding to avoid direct infant exposure to NATROBA [see Use in Specific Populations (8.2)]

Patient Information for Head Lice Treatment
NATROBA™ (Nah-TRO-buh)
(spinosad)
topical suspension

Important: For use on scalp hair and scalp only. Do not get NATROBA in your eyes, mouth, or vagina.

What is NATROBA?
NATROBA is a prescription medicine used to treat head lice on the scalp and hair of adults and children 6 months of age and older.
It is not known if NATROBA is safe and effective for children under 6 months of age.
See "How do I stop the spread of lice?" at the end of this leaflet for additional information on ways to stop the spread of lice.

Before you use NATROBA, tell your healthcare provider about all of your medical conditions, including if you or your child:

- have any skin conditions or sensitivities
- are pregnant or plan to become pregnant. It is not known if NATROBA can harm your unborn baby.
- are breastfeeding or plan to breastfeed. Talk to your healthcare provider about the best way to feed your baby during treatment with NATROBA.

How should I use NATROBA?

- See the detailed "Instructions for Use" at the end of this leaflet.
- Apply NATROBA exactly as prescribed by your healthcare provider. Your healthcare provider will prescribe the treatment that is right for you. Do not change your treatment unless you talk to your healthcare provider.
- Apply NATROBA when your hair is dry. Do not wet your hair before applying NATROBA.
- It is important to apply enough NATROBA to completely coat all of your hair and scalp. Leave NATROBA on your hair and scalp for a full 10 minutes.
- If live lice are seen one week (7 days) after you applied NATROBA, you will need to apply NATROBA again.
- Because you need to completely cover all of the lice with NATROBA, you may need help in applying NATROBA to your scalp and hair.
- Children will need an adult to apply NATROBA for them.
- Do not get NATROBA into your eyes. If NATROBA gets in your eye, rinse well with water right away.
- If you have any scalp irritation after you apply NATROBA, call your healthcare provider right away.
- Wash your hands after you apply NATROBA.
- Do not swallow NATROBA. If swallowed, call Poison Control at 1-800-222-1222 or go to the nearest emergency room right away.

What are the possible side effects of NATROBA?
The most common side effects of NATROBA include redness where NATROBA is applied and redness to eyes.
These are not all the possible side effects of NATROBA.
Call your doctor for medical advice about side effects. You may report side effects to FDA at 1-800-FDA-1088.

How should I store NATROBA?

- Store NATROBA at room temperature between 68°F to 77°F (20°C to 25°C).

Keep NATROBA and all medicines out of the reach of children.

General information about the safe and effective use of NATROBA.
Medicines are sometimes prescribed for purposes other than those listed in a Patient Information leaflet. Do not use NATROBA for a condition for which it was not prescribed. Do not give NATROBA to other people, even if they have the same symptoms that you have. It may harm them. You can ask your pharmacist or healthcare provider for information about NATROBA that is written for health professionals.

What are the ingredients in NATROBA?
Active ingredient: Spinosad
Inactive ingredients: Benzyl Alcohol, Butylated Hydroxytoluene, Ceteareth-20, Cetearyl Alcohol, FD&C Yellow #6, Hexylene Glycol, Hydroxyethyl Cellulose, Isopropyl Alcohol, Propylene Glycol, Stearalkonium Chloride, Water, Hydrochloric acid (HCl) as pH adjuster.

Instructions for Use

Before you use NATROBA, it is important that you read this Instructions for Use. Be sure that you read, understand, and follow this Instructions for Use so that you use NATROBA the right way. Ask your healthcare provider or pharmacist if you have questions about the right way to use NATROBA.

Important information:

- Your hair and scalp must be dry before applying NATROBA.
- For very thick, medium length hair or long hair, an entire bottle (120mL) of NATROBA may be needed to cover the scalp and hair. Less NATROBA may be needed for shorter, thinner hair.

How to apply NATROBA to your scalp and hair:

Step 1

- Shake NATROBA bottle well right before use.

Step 2

- Cover your face and eyes with a towel and keep your eyes closed tightly.
- Apply NATROBA directly to dry hair and scalp.
- Completely cover the scalp and hair closest to the scalp first, and then apply outwards towards the ends of the hair.
- It is important to apply enough NATROBA to cover your entire scalp and hair so that all lice and eggs are exposed to NATROBA.

Step 3

- Allow NATROBA to stay on your scalp and hair for 10 minutes. Use a timer or clock and start timing after you have completely covered your hair and scalp with NATROBA.
- Continue to keep eyes covered to prevent dripping into your eyes.
- After 10 minutes, completely rinse NATROBA from your hair and scalp with warm water.
- You may use a fine-tooth comb to remove treated lice and nits from the hair and scalp, but combing is not required.
- Wash your hands after applying NATROBA.
- It is okay to shampoo your hair any time after the treatment.

If you see live lice on your scalp or hair one week (7 days), after your first treatment, repeat the steps above.

How do I stop the spread of lice?

To help prevent the spread of lice from one person to another, here are some steps you can take:

- Avoid direct head-to-head contact with anyone known to have live, crawling lice.
- Do not share combs, brushes, hats, scarves, bandannas, ribbons, barrettes, hair bands, towels, helmets, or other hair-related personal items with anyone else, whether they have lice or not.
- Avoid sleepovers and slumber parties during lice outbreaks. Lice can live in bedding, pillows, and carpets that have recently been used by someone with lice.
- After finishing treatment with lice medicine, check everyone in your family for lice after one week. Be sure to talk to your healthcare provider about treatments for those who have lice.
- Machine-wash or dry-clean any bedding, towels and clothing used by anyone having lice. Machine-wash at high temperatures (150°F) and tumble in a hot dryer for 20 minutes.
- Wash personal items such as combs, brushes, and hair clips in hot water.

Distributed by: Cipher Pharmaceuticals US LLC, Carmel, IN 46032

This Patient Information and Instructions for Use have been approved by the U.S. Food and Drug Administration.

Revised: 6/2025

Patient Information for Scabies Treatment
NATROBA™ (Nah-TRO-buh)
(spinosad)
topical suspension

Important: For use on skin only. Do not get NATROBA in your eyes, mouth, or vagina.

What is NATROBA?
NATROBA is a prescription medicine used to treat scabies in adults and children 4 years of age and older.
It is not known if NATROBA is safe and effective in children under 4 years of age.
See "How do I stop the spread of scabies?" at the end of this leaflet.

Before you use NATROBA, tell your healthcare provider about all of your medical conditions, including if you or your child:

- have any skin conditions or sensitivities
- are pregnant or plan to become pregnant. It is not known if NATROBA can harm your unborn baby.
- are breastfeeding or plan to breastfeed. Wash the breast area with soap and water to remove NATROBA before breastfeeding to avoid exposure to your baby. Talk to your healthcare provider about the best way to feed your baby during treatment with NATROBA.

How should I use NATROBA?

- See the detailed "Instructions for Use" at the end of this leaflet.
- Apply NATROBA exactly as prescribed by your healthcare provider. Your healthcare provider will prescribe the treatment that is right for you. Do not change your treatment unless you talk to your healthcare provider.
- It is important to apply enough NATROBA to completely cover your body from your neck to the soles of your feet. Make sure you apply to folds of skin, between fingers and toes, and under finger and toe nails.
- If you are balding, apply NATROBA to the scalp, hairline, temples, and forehead.
- Wait a full 10 minutes to allow NATROBA to soak into the skin and dry before getting dressed. Leave NATROBA on the skin for at least 6 hours before showering or bathing.
- Because you need to completely cover your body from the neck down with NATROBA, you may need help in applying NATROBA to ensure full coverage.
- Children will need an adult to apply NATROBA for them.
- Do not get NATROBA into your eyes. If NATROBA gets in your eye, rinse well with water right away.
- If you have any skin irritation after you apply NATROBA, call your healthcare provider right away.
- Wash your hands after applying NATROBA to someone else.
- Do not swallow NATROBA. If swallowed, call Poison Control at 1-800-222-1222 or go to the nearest emergency room right away.

What are the possible side effects of NATROBA?
The most common side effects of NATROBA include irritation (including pain and burning) at application sites and dry skin.
These are not all the possible side effects of NATROBA.
Call your doctor for medical advice about side effects. You may report side effects to FDA at 1-800-FDA-1088.

How should I store NATROBA?

- Store NATROBA at room temperature between 68°F to 77°F (20°C to 25°C).

Keep NATROBA and all medicines out of the reach of children.

General information about the safe and effective use of NATROBA.
Medicines are sometimes prescribed for purposes other than those listed in a Patient Information leaflet. Do not use NATROBA for a condition for which it was not prescribed. Do not give NATROBA to other people, even if they have the same symptoms that you have. It may harm them. You can ask your pharmacist or healthcare provider for information about NATROBA that is written for health professionals.

What are the ingredients in NATROBA?
Active ingredient: spinosad
Inactive ingredients: Benzyl Alcohol, Butylated Hydroxytoluene, Ceteareth-20, Cetearyl Alcohol, FD&C Yellow #6, Hexylene Glycol, Hydroxyethyl Cellulose, Isopropyl Alcohol, Propylene Glycol, Stearalkonium Chloride, Water, Hydrochloric acid (HCl) as pH adjuster.

Instructions for Use

Before you use NATROBA, it is important that you read this Instructions for Use. Be sure that you read, understand, and follow this Instructions for Use so that you use NATROBA the right way. Ask your healthcare provider or pharmacist if you have questions about the right way to use NATROBA.

How to apply NATROBA to your body:

Step 1

- Shake the NATROBA bottle well right before use.

Step 2

Figure A

Figure B

Figure C

- Apply NATROBA to the skin. (See Figure A)
- Apply enough NATROBA to completely cover your body from your neck to the soles of your feet. (See Figure B). Make sure you apply to folds of skin, between fingers and toes, and under finger and toe nails. (See Figure C)
- If you are balding, you should also apply NATROBA to the scalp, hairline, temples and forehead.
- You may need help applying NATROBA to ensure full coverage.
- If you do not completely cover your body with NATROBA, some scabies mites may escape treatment.
- Wash your hands after applying NATROBA to someone else.

Step 3

Figure D

Figure E

Figure F

- Allow NATROBA to soak into the skin and dry for 10 minutes. Use a timer or clock and start timing after you have completely covered your body with NATROBA. (See Figure D)
- After 10 minutes, you can get dressed. (See Figure E)
- Wait at least 6 hours before showering or bathing. (See Figure F)

How do I stop the spread of scabies?

To help prevent the spread of scabies from one person to another, here are some steps you can take:

- Get household members checked by their healthcare provider.
- Avoid direct body-to-body contact with anyone known to have scabies, including sexual partners.
- Do not share clothing, towels, bedding or linens with anyone else. The scabies mite can live in bedding, pillows, and carpets that have recently been used by someone with scabies.
- Machine-wash or dry clean any bedding, clothing and towels that you have used anytime during the three days before treatment by washing in hot water and drying in a hot dryer, or by sealing in a plastic bag for at least 72 hours. Machine-wash at high temperatures (150°F) and tumble in a hot dryer for 20 minutes.

Distributed by: Cipher Pharmaceuticals US LLC, Carmel, IN 46032

NAT-PI-003

This Patient Information and Instructions for Use have been approved by the U.S. Food and Drug Administration.

Issued: 6/2025

PRINCIPAL DISPLAY PANEL - 120 mL Bottle Carton

NDC 84635-929-04

120 mL

Rx only

Natroba™
(spinosad)
Topical Suspension
0.9%

For topical use only